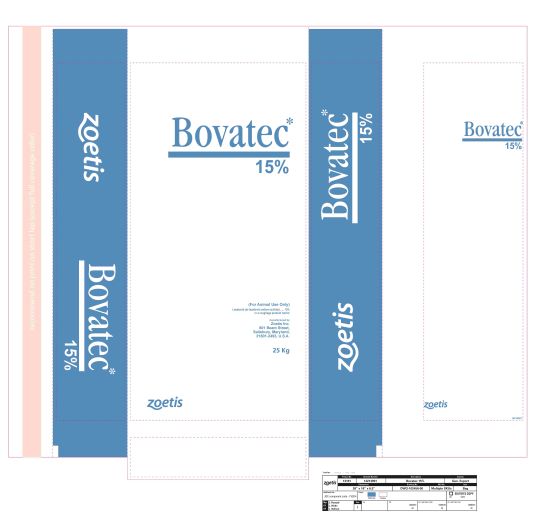 DRUG LABEL: Bovatec 15%
NDC: 66104-9985 | Form: POWDER
Manufacturer: Phibro Animal Health
Category: animal | Type: OTC ANIMAL DRUG LABEL
Date: 20250310

ACTIVE INGREDIENTS: LASALOCID SODIUM 90.7 g/0.45 kg

Bovatec 15% (Lasalocid Sodium)

DESCRIPTION

Bovatec 15% (Lasalocid Sodium)

INDICATIONS AND USAGE

Use directions
Species Dose Indications for use

Cattle Fed in Confinement for Slaughter:

Dose: 10-30 grams lasalocid per ton of total ration (90% dray matter)

Indications for Use: For improved feed efficiency in cattle fed in confinement for slaughter, feed continuously to provide not less than 100 mg no
more than 360 mg per head per day.

Dose: 25-30 grams lasalocid per ton of total ration (90% dry matter)

Indications: For improved feed efficiency and increased rate of weight gain in cattle fed in confinement for slaughter, feed continuously to
provide not less than 250 mg not more than 360 mg per head per day.

Pasture Cattle – slaughter, stocker, feeder cattle, and dairy and beef replacement heifers:

Dose: 60-300 mg lasalocid per head/day

Indications: For increased rate of weight gain. The drug must be contained in at least 1 pound of feed and fed continuously on a daily basis.

Dose: 60-300 mg lasalocid per head/day

Indications: For increased rate of weight gain, feed continuously on a free-choice basis. A medicated feed mill license is required when free choice
feed is manufactured using a proprietary formula and/or specifications. Free-choice feed formulations must be FDA-approved.

Daily lasalocid intakes in excess of 200 mg per head per day have not been shown to be more effective than 200 mg lasalocid per head per day.

NOTE: Coccidiosis may occur when young pasture cattle are co-mingled with adult cattle passing coccidial oocysts.

Cattle:

Dose: 1 mg lasalocid per 2.2 lbs body weight/day

Indications: For control of coccidiosis caused by Eimeria bovis and E. zuernii in cattle up to 800 lbs. Hand feed continuously to provide not more
than 360 mg per day.

Sheep:

Dose: 20-30 grams lasalocid per ton of total ration (90% dry matter)

Indications: For prevention of coccidiosis caused by Eimeria ovina, E. crandallis, E. ovinoidalis (E. ninakohlyakimovae), E. parva, and E. intricata in sheep maintained in confinement. Feed continuously to provide not less than 15 mg nor more than 70 mg per head per day depending on body weight.

Bovatec 15